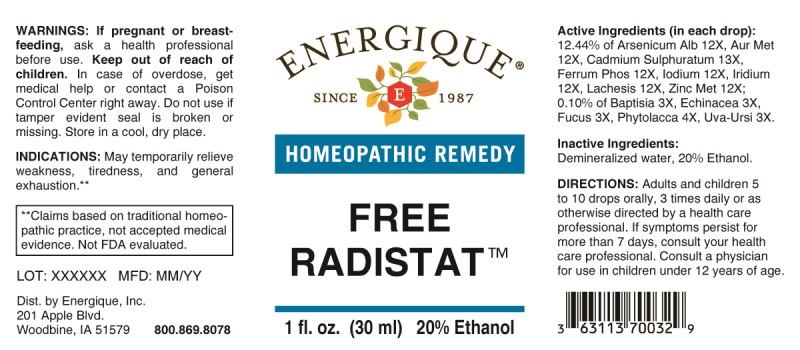 DRUG LABEL: Free Radistat
NDC: 44911-0464 | Form: LIQUID
Manufacturer: Energique, Inc.
Category: homeopathic | Type: HUMAN OTC DRUG LABEL
Date: 20240422

ACTIVE INGREDIENTS: BAPTISIA TINCTORIA ROOT 3 [hp_X]/1 mL; ECHINACEA ANGUSTIFOLIA WHOLE 3 [hp_X]/1 mL; FUCUS VESICULOSUS 3 [hp_X]/1 mL; ARCTOSTAPHYLOS UVA-URSI LEAF 3 [hp_X]/1 mL; PHYTOLACCA AMERICANA ROOT 4 [hp_X]/1 mL; ARSENIC TRIOXIDE 12 [hp_X]/1 mL; GOLD 12 [hp_X]/1 mL; FERROSOFERRIC PHOSPHATE 12 [hp_X]/1 mL; IODINE 12 [hp_X]/1 mL; IRIDIUM 12 [hp_X]/1 mL; LACHESIS MUTA VENOM 12 [hp_X]/1 mL; ZINC 12 [hp_X]/1 mL; CADMIUM SULFIDE 13 [hp_X]/1 mL
INACTIVE INGREDIENTS: WATER; ALCOHOL

DRUG FACTS:

ACTIVE INGREDIENTS:

(in each drop): 12.44% of Arsenicum Album 12X, Aurum Metallicum 12X, Cadmium Sulphuratum 13X, Ferrum Phosphoricum 12X, Iodium 12X, Iridium Metallicum 12X, Lachesis Mutus 12X, Zincum Metallicum 12X; 0.10% of Baptisia Tinctoria 3X, Echinacea (Angustifolia) 3X, Fucus Vesiculosus 3X, Phytolacca Decandra 4X, Uva-Ursi 3X.

INDICATIONS:

May temporarily relieve weakness, tiredness, and general exhaustion.**

**Claims based on traditional homeopathic practice, not accepted medical evidence. Not FDA evaluated.

WARNINGS:

If pregnant or breast-feeding, ask a health professional before use.

Keep out of reach of children. In case of overdose, get medical help or contact a Poison Control Center right away.

Do not use if tamper evident seal is broken or missing. Store in a cool, dry place.

KEEP OUT OF REACH OF CHILDREN:

In case of overdose, get medical help or contact a Poison Control Center right away.

DIRECTIONS:

Adults and children 5 to 10 drops orally, 3 times daily or as otherwise directed by a health care professional. If symptoms persist for more than 7 days, consult your health care professional. Consult a physician for use in children under 12 years of age.

INDICATIONS:

May temporarily relieve weakness, tiredness, and general exhaustion.**
**Claims based on traditional homeopathic practice, not accepted medical evidence. Not FDA evaluated.

INACTIVE INGREDIENTS:

Demineralized water, 20% Ethanol.

QUESTIONS:

Dist. by Energique, Inc.

201 Apple Blvd

Woodbine, IA 51579 800.869.8078

PACKAGE LABEL DISPLAY:

ENERGIQUE

SINCE 1987

HOMEOPATHIC REMEDY

FREE RADISTAT

1 fl. oz. (30 ml)